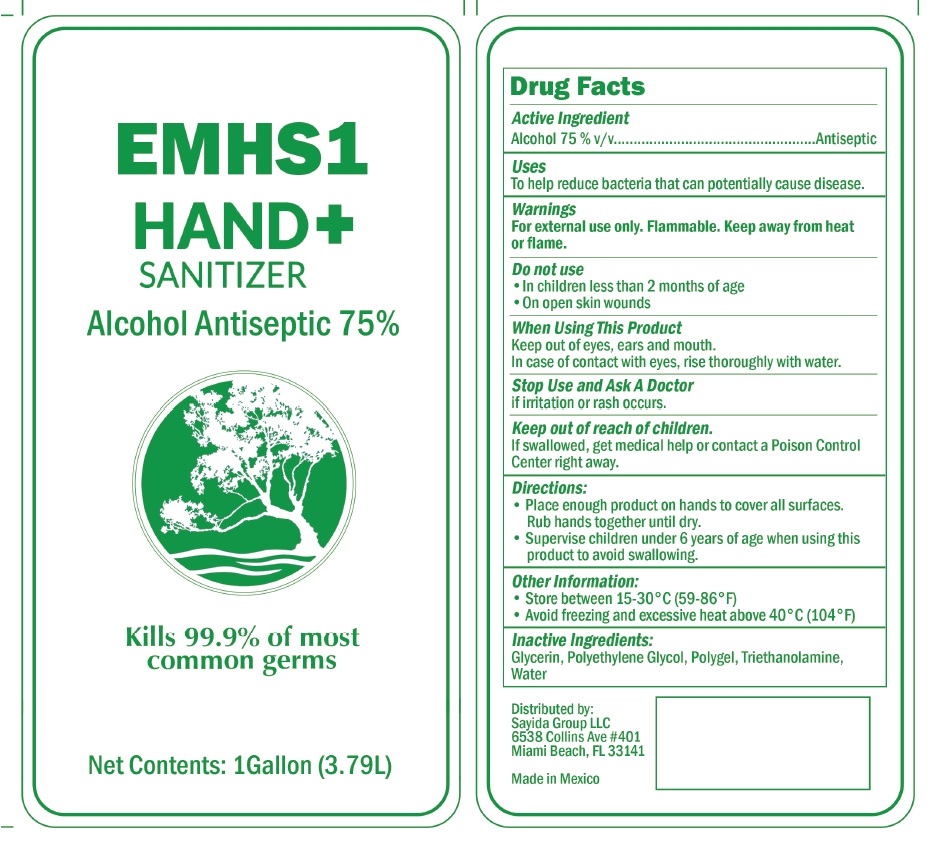 DRUG LABEL: EMHS1 Hand Sanitizer
NDC: 77858-0750 | Form: GEL
Manufacturer: Sayida Group, LLC
Category: otc | Type: HUMAN OTC DRUG LABEL
Date: 20200520

ACTIVE INGREDIENTS: ALCOHOL 75 L/100 L
INACTIVE INGREDIENTS: GLYCERIN; WATER; POLYGELINE; TROLAMINE; POLYETHYLENE GLYCOL, UNSPECIFIED

EMHS1 Hand Sanitizer (Ethanol)

Active Ingredient(s)

Alcohol 75% v/v.

Purpose

Antiseptic, Hand Sanitizer

Use

To help reduce bacteria that potentially can cause disease.

Warnings

For external use only. Flammable. Keep away from heat or flame

Do not use

- in children less than 2 months of age
- on open skin wounds

When using this product keep out of eyes, ears, and mouth. In case of contact with eyes, rinse eyes thoroughly with water.

Stop use and ask a doctor if irritation or rash occurs.

Keep out of reach of children. If swallowed, get medical help or contact a Poison Control Center right away.

Directions

- Place enough product on hands to cover all surfaces. Rub hands together until dry.
- Supervise children under 6 years of age when using this product to avoid swallowing.

Other information

- Store between 15-30C (59-86F)
- Avoid freezing and excessive heat above 40C (104F)

Inactive ingredients

Glycerin, Polyethylene Glycol, Polygel, Triethanolamine, Water

Package Label - Principal Display Panel

3.79L (1 Gal) NDC: 77858-0750-1

Distributed by:
Sayida Group LLC
6538 Collins Ave #401
Miami Beach, FL 33141
Made in Mexico